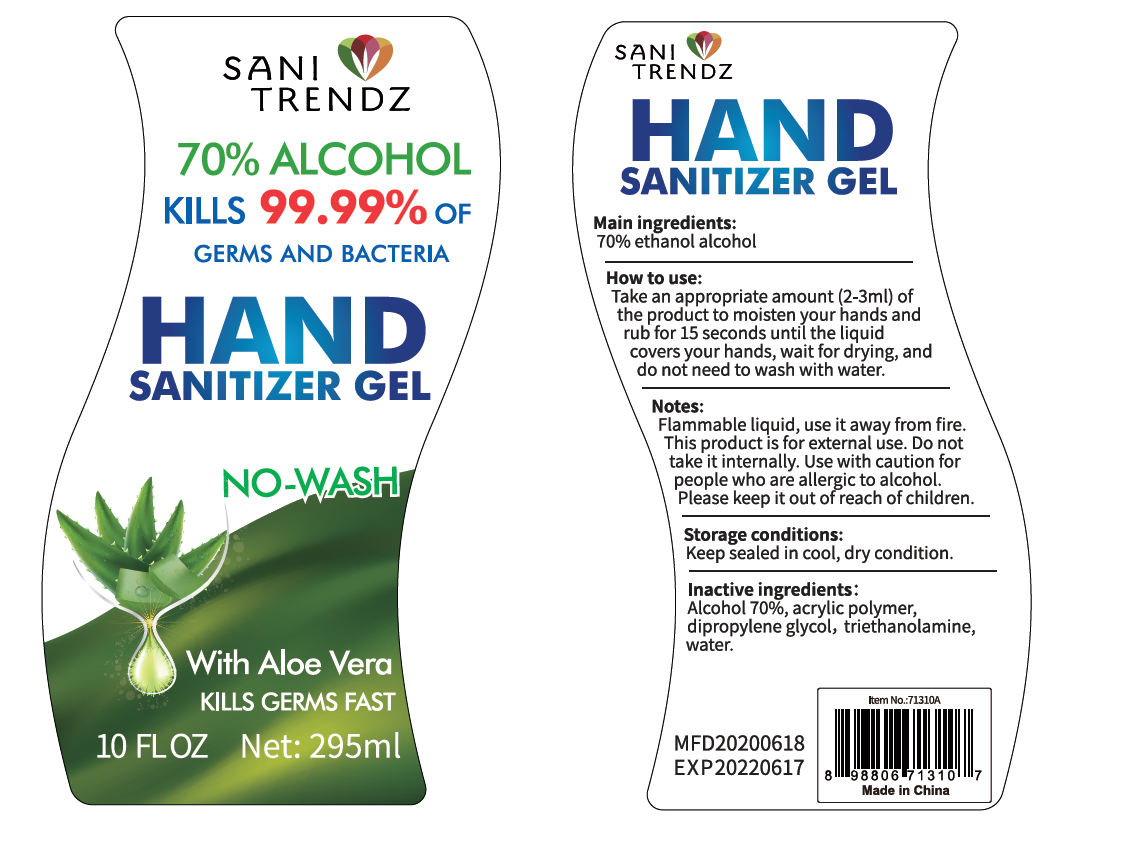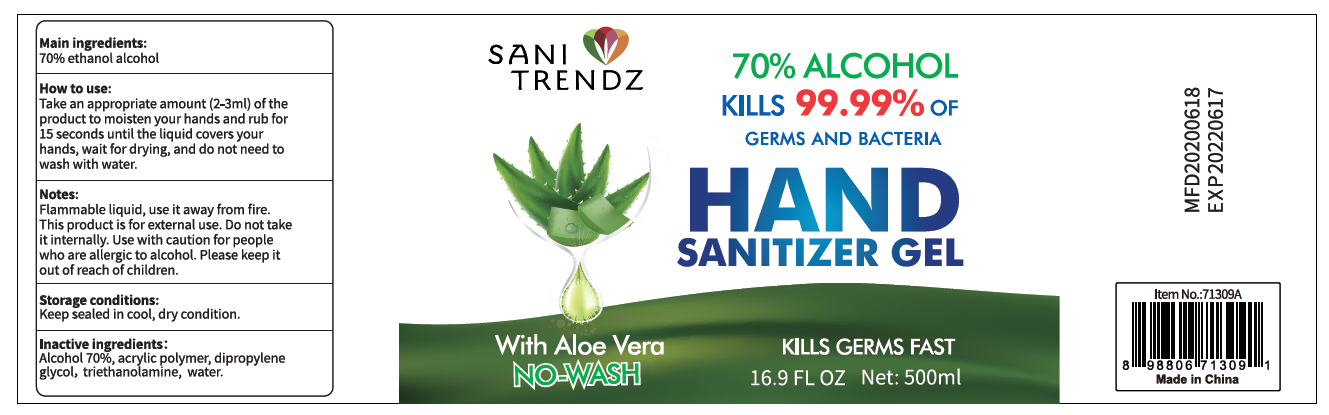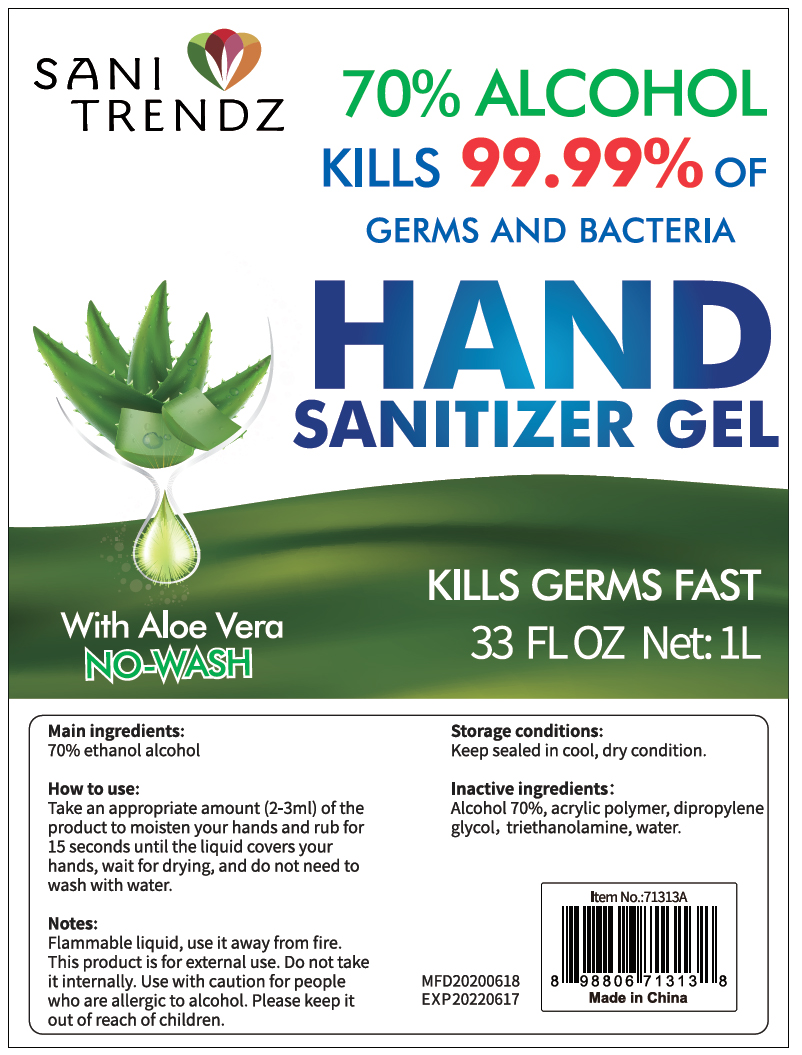 DRUG LABEL: 70% alcohol hand sanitizer (no water)
NDC: 75021-002 | Form: GEL
Manufacturer: D Zone Imports, Llc
Category: otc | Type: HUMAN OTC DRUG LABEL
Date: 20230213

ACTIVE INGREDIENTS: ALCOHOL 70 mL/100 mL
INACTIVE INGREDIENTS: DIPROPYLENE GLYCOL; CARBOMER 940; WATER; TROLAMINE

70% alcohol hand sanitizer (no water)

Active ingredient

Alcohol 70% v/v. Purpose: Antiseptic

Purpose

Antiseptic. Hand senitizer

INDICATIONS AND USAGE

Hand sanitizer gel, kills 99.99% BACTERIA

Directions

Take an appropriate amount (2-3ml) of the product to moisten your hands and rub for 15 seconds until the liquid covers your hands, wait for drying, and do not need to wash with water

Warnings

Flammable liquid, use it sawy from fire. This product is for external use.

Do not use

Do not take it internally. Use with caution to people who are allergic to alcohol.

Please keep it out of reach of children

STOP USE

Use with caution to people who are allergic to alcohol

WHEN USING

Do not take it internally

Inactive ingredients

Acrylic polymer, dipropylene glycol, triethanolamine, water

Storage condition

Keep sealed in cool, dry condition

Package Label - Principal Display Panel

295 mL NDC: 75021-002-01

SANI

TRENDZ

70% ALCOHOL

KILLS 99.99% OF

GERMS AND BACTERIA

HAND

SANITIZER GEL

NO-WASH

WITH ALOE VERA

KILLS GERMS FAST

10 FZ OZ Net: 295ml

500 mL NDC: 75021-002-02

SANI

TRENDZ

70% ALCOHOL

KILLS 99.99% OF

GERMS AND BACTERIA

HAND

SANITIZER GEL

NO-WASH

WITH ALOE VERA

KILLS GERMS FAST

16.9 FZ OZ Net: 500ml

1000 mL NDC: 75021-002-03

SANI

TRENDZ

70% ALCOHOL

KILLS 99.99% OF

GERMS AND BACTERIA

HAND

SANITIZER GEL

NO-WASH

WITH ALOE VERA

KILLS GERMS FAST

33 FZ OZ Net: 1L